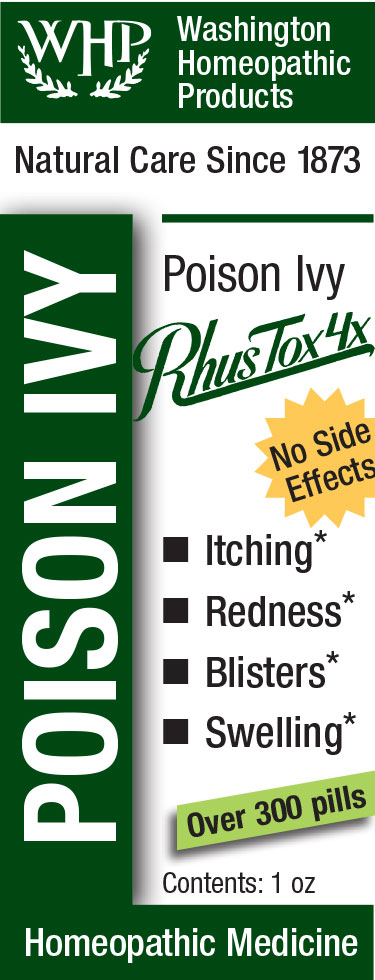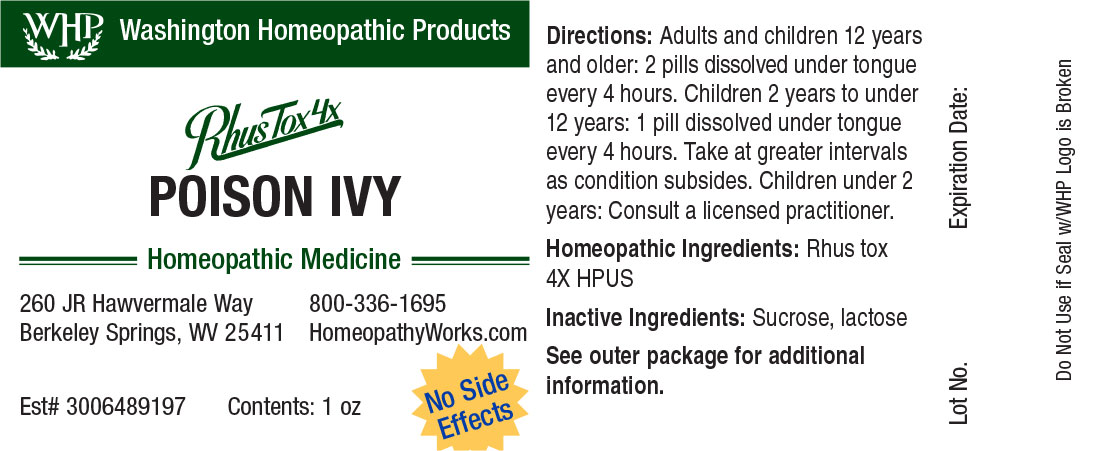 DRUG LABEL: WHP Poison Ivy
NDC: 71919-823 | Form: PELLET
Manufacturer: Washington Homeopathic Products
Category: homeopathic | Type: HUMAN OTC DRUG LABEL
Date: 20260108

ACTIVE INGREDIENTS: TOXICODENDRON PUBESCENS LEAF 4 [hp_X]/1 1
INACTIVE INGREDIENTS: SUCROSE; LACTOSE, UNSPECIFIED FORM

WHP Poison Ivy

ACTIVE INGREDIENT

RHUS TOX 4X

USES

To relieve the symptoms of conditions produced by Poison Oak and Poison Ivy

KEEP OUT OF REACH OF CHILDREN

As with all medications, keep out of reach of children.

INDICATIONS

Rhus Tox Better motion

STOP USE AND ASK DOCTOR

If symptoms persist or recur, discontinue use. If pregnant or nursing, consult a licensed practitioner before using this product.

DIRECTIONS

Directions: Adults and children 12 years and older: 2 pills dissolved under tongue every 4 hours, or as directed by a licensed practitioner. Children 4 years to under 12 years: 1 pill dissolved under tongue every 4 hours, or as directed by a licensed practitioner. Children under 4 years: Consult a licensed practitioner.

INACTIVE INGREDIENTS

Sucrose/Lactose